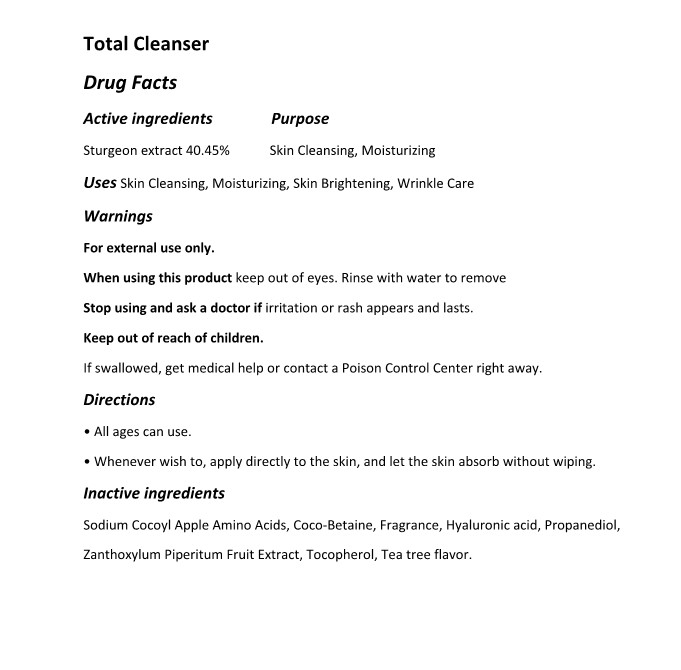 DRUG LABEL: The Zoeun Skin Total Cleanser
NDC: 83636-601 | Form: SOLUTION
Manufacturer: Sturgeonbio Co.,Ltd.
Category: otc | Type: HUMAN OTC DRUG LABEL
Date: 20250120

ACTIVE INGREDIENTS: STURGEON, UNSPECIFIED 40.45 g/100 mL
INACTIVE INGREDIENTS: HYALURONIC ACID; SODIUM COCOYL APPLE AMINO ACIDS; ZANTHOXYLUM PIPERITUM FRUIT PULP; COCAMIDOPROPYL BETAINE; TOCOPHEROL; FRAGRANCE 13576; PROPANEDIOL; MELALEUCA ALTERNIFOLIA (TEA TREE) LEAF OIL

83636-601 The Zoeun Skin Total Cleanser

Active Ingredients

Sturgeon extract 40.45%

Purposes

Skin Cleansing, Moisturizing

Uses

Skin Cleansing, Moisturizing, Skin Brightening, Wrinkle Care

Warnings

Keep out of reach of children.
If swallowed, get medical help or contact a Poison Control Center right away.

Warnings

Stop using and ask a doctor if irritation or rash appears and lasts.

Warnings

When using this product keep out of eyes. Rinse with water to remove

Warnings

For external use only.

Directions

• All ages can use.
• Whenever wish to, apply directly to the skin, and let the skin absorb without wiping.

Inactive Ingredients

Sodium Cocoyl Apple Amino Acids, Coco-Betaine, Fragrance, Hyaluronic acid, Propanediol, Zanthoxylum Piperitum Fruit Extract, Tocopherol, Tea tree flavor